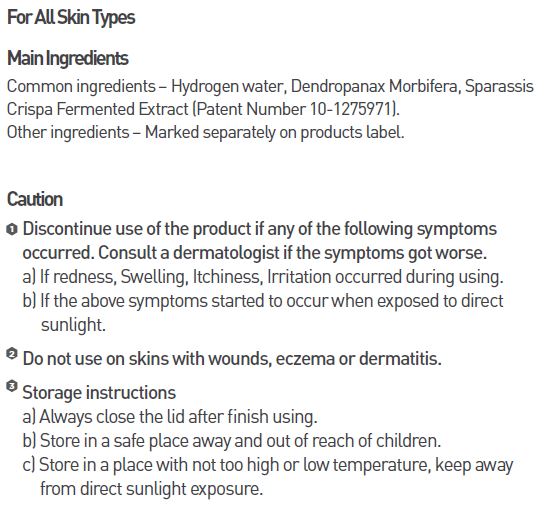 DRUG LABEL: MEDI HYDRO DP
NDC: 70694-0007 | Form: EMULSION
Manufacturer: Inc MBG
Category: otc | Type: HUMAN OTC DRUG LABEL
Date: 20190124

ACTIVE INGREDIENTS: GLYCERIN 6 g/100 mL
INACTIVE INGREDIENTS: WATER; BUTYLENE GLYCOL

INDICATIONS AND USAGE

Apply enough amount softly on the whole face and allow it to absorb, every day and night after toner

Keep out of reach of children.

DOSAGE AND ADMINISTRATION

for external use only

WARNINGS

Discontinue use of the product if any of the following symptoms occurred. Consult a dermatologist if the symptoms got worse.
a) If redness, Swelling, Itchiness, Irritation occurred during using.
b) If the above symptoms started to occur when exposed to direct sunlight.
Do not use on skins with wounds, eczema or dermatitis.

Storage instructions
a) Always close the lid after finish using.
b) Store in a safe place away and out of reach of children.
c) Store in a place with not too high or low temperature, keep awayfrom direct sunlight exposure.

PURPOSE

Provides balanced sebum and moistures to make skin pure and soft

INACTIVE INGREDIENT

water, butylene glycol, niacinamide, etc.

ACTIVE INGREDIENT

glycerin